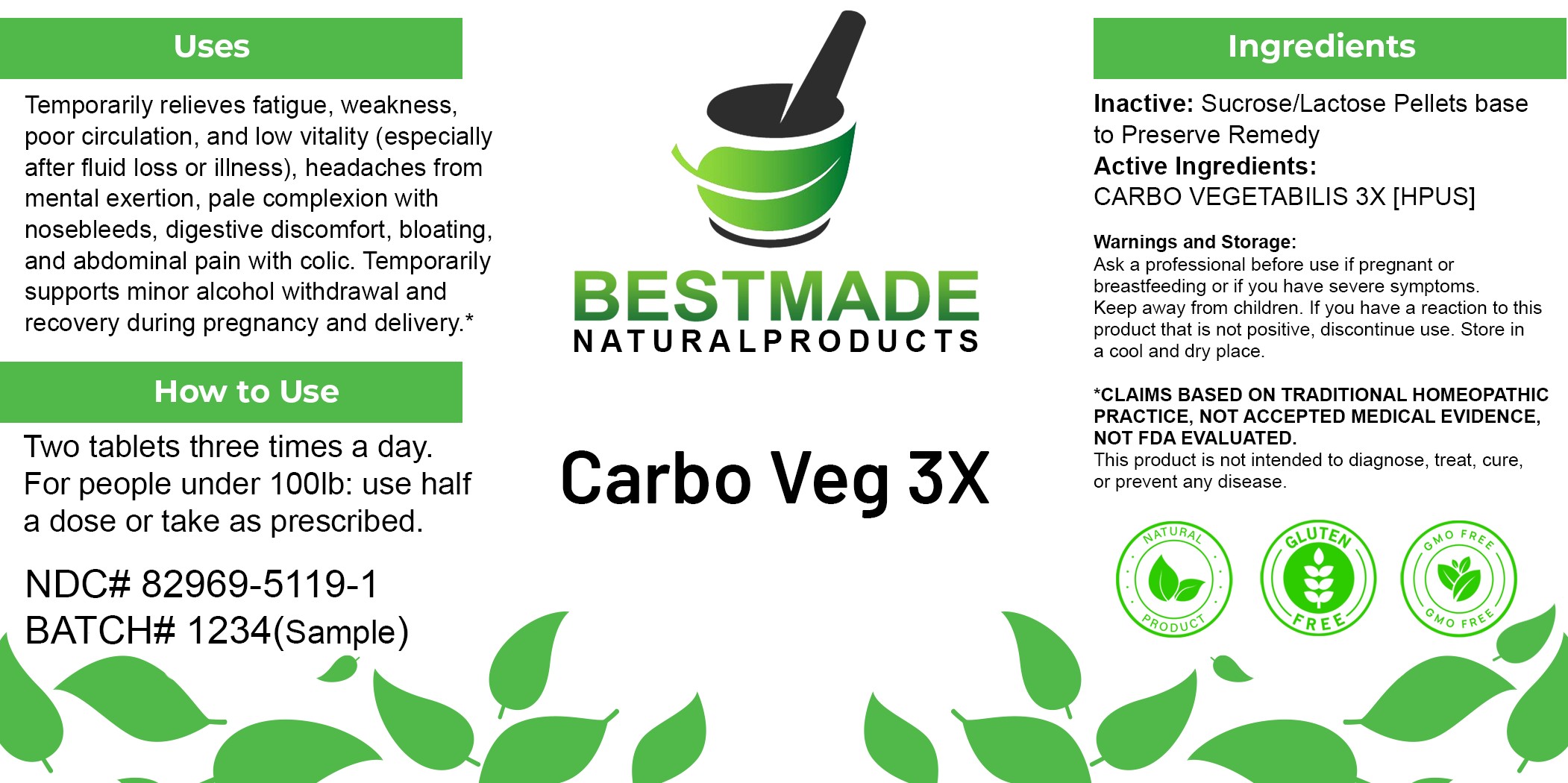 DRUG LABEL: Bestmade Natural Products Carbo Veg 3X
NDC: 82969-5119 | Form: TABLET
Manufacturer: Bestmade Natural Products
Category: homeopathic | Type: HUMAN OTC DRUG LABEL
Date: 20250605

ACTIVE INGREDIENTS: ACTIVATED CHARCOAL 3 [hp_X]/62.5 mg
INACTIVE INGREDIENTS: LACTOSE 61.56 mg/62.5 mg

Carbo Veg 3X

Inactive Ingredient: Lactose base to preserve the product

INDICATIONS AND USAGE

Use: Temporarily relieves fatigue, weakness, poor circulation, and low vitality (especially after fluid loss or illness), headaches from mental exertion, pale complexion with nosebleeds, digestive discomfort, bloating, and abdominal pain with colic. Temporarily supports minor alcohol withdrawal and recovery during pregnancy and delivery.*

PURPOSE

Use: Temporarily relieves fatigue, weakness, poor circulation, and low vitality (especially after fluid loss or illness), headaches from mental exertion, pale complexion with nosebleeds, digestive discomfort, bloating, and abdominal pain with colic. Temporarily supports minor alcohol withdrawal and recovery during pregnancy and delivery.*

DOSAGE AND ADMINISTRATION

Dosage instructions: Two tablets three times a day. For people under 100lb: use half a dose or take as prescribed.

Active Ingredient: CARBO VEGETABILIS 3X [HPUS]

KEEP OUT OF REACH OF CHILDREN

Warnings and Storage:

Ask a professional before use if pregnant or breastfeeding or if you have severe symptoms. Keep away from children. If you have a reaction to this product that is not positive, discontinue use. Store in a cool and dry place.

*CLAIMS BASED ON TRADITIONAL HOMEOPATHIC PRACTICE, NOT ACCEPTED MEDICAL EVIDENCE, NOT FDA EVALUATED. This product is not intended to diagnose, treat, cure, or prevent any disease.

Warnings and Storage:

Ask a professional before use if pregnant or breastfeeding or if you have severe symptoms. Keep away from children. If you have a reaction to this product that is not positive, discontinue use. Store in a cool and dry place.

*CLAIMS BASED ON TRADITIONAL HOMEOPATHIC PRACTICE, NOT ACCEPTED MEDICAL EVIDENCE, NOT FDA EVALUATED. This product is not intended to diagnose, treat, cure, or prevent any disease.

Entire package label.